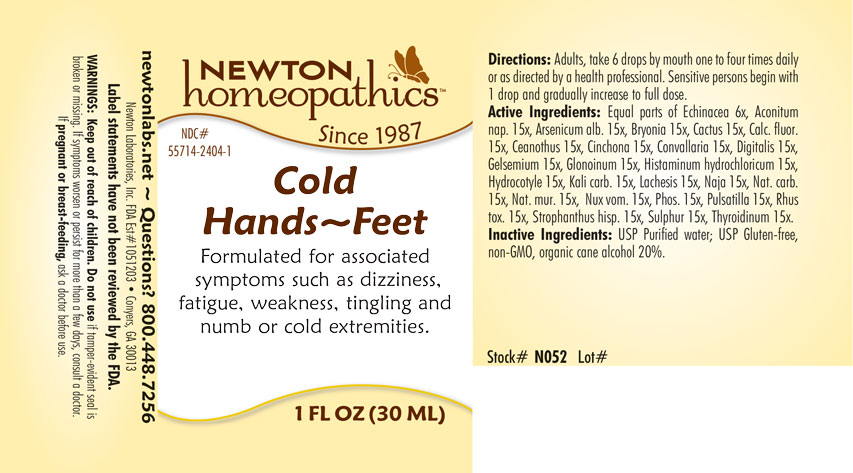 DRUG LABEL: Cold Hands - Feet
NDC: 55714-2404 | Form: LIQUID
Manufacturer: Newton Laboratories, Inc.
Category: homeopathic | Type: HUMAN OTC DRUG LABEL
Date: 20201124

ACTIVE INGREDIENTS: HISTAMINE DIHYDROCHLORIDE 15 [hp_X]/1 mL; THYROID, UNSPECIFIED 15 [hp_X]/1 mL; ACONITUM NAPELLUS 15 [hp_X]/1 mL; ARSENIC TRIOXIDE 15 [hp_X]/1 mL; BRYONIA ALBA ROOT 15 [hp_X]/1 mL; SELENICEREUS GRANDIFLORUS STEM 15 [hp_X]/1 mL; CALCIUM FLUORIDE 15 [hp_X]/1 mL; CEANOTHUS AMERICANUS LEAF 15 [hp_X]/1 mL; CINCHONA OFFICINALIS BARK 15 [hp_X]/1 mL; CONVALLARIA MAJALIS 15 [hp_X]/1 mL; DIGITALIS 15 [hp_X]/1 mL; GELSEMIUM SEMPERVIRENS ROOT 15 [hp_X]/1 mL; NITROGLYCERIN 15 [hp_X]/1 mL; CENTELLA ASIATICA 15 [hp_X]/1 mL; POTASSIUM CARBONATE 15 [hp_X]/1 mL; LACHESIS MUTA VENOM 15 [hp_X]/1 mL; NAJA NAJA VENOM 15 [hp_X]/1 mL; SODIUM CARBONATE 15 [hp_X]/1 mL; SODIUM CHLORIDE 15 [hp_X]/1 mL; STRYCHNOS NUX-VOMICA SEED 15 [hp_X]/1 mL; PHOSPHORUS 15 [hp_X]/1 mL; PULSATILLA VULGARIS 15 [hp_X]/1 mL; TOXICODENDRON PUBESCENS LEAF 15 [hp_X]/1 mL; STROPHANTHUS HISPIDUS SEED 15 [hp_X]/1 mL; SULFUR 15 [hp_X]/1 mL; ECHINACEA, UNSPECIFIED 6 [hp_X]/1 mL
INACTIVE INGREDIENTS: ALCOHOL; WATER

Cold Hands 2404L

WARNINGS SECTION

WARNINGS: Keep out of reach of children. Do not use if tamper-evident seal is broken or missing. If symptoms worsen or persist for more than a few days, consult a doctor. If pregnant or breast-feeding, ask a doctor before use.

OTC - KEEP OUT OF REACH OF CHILDREN SECTION

Keep out of reach of children.

DOSAGE & ADMINISTRATION SECTION

Adults, take 6 drops by mouth one to four times daily or as directed by a health professional. Sensitive persons begin with 1 drop and gradually increase to full dose.

OTC - ACTIVE INGREDIENT SECTION

Equal parts of Echinacea 6x, Aconitum nap. 15x, Arsenicum alb. 15x, Bryonia 15x, Cactus 15, Calc. fluor. 15x, Ceanothus 15x, Cinchona 15x, Convallaria 15x, Digitalis 15x, Gelsemium 15x, Glonoinum 15x, Histaminum hydrochloricum 15x, Hydrocotyle 15x, Kali carb. 15x, Lachesis 15x, Naja 15x, Nat. carb. 15x, Nat. mur. 15x, Nux vom. 15x, Phos. 15x, Pulsatilla 15x, Rhus tox. 15x, Strophanthus hisp. 15x, Sulphur 15x, Thyroidinum 15x.

OTC - PURPOSE SECTION

Formulated for associated symptoms such as dizziness, fatigue, weakness, tingling and numb or cold extremities.

INACTIVE INGREDIENT SECTION

USP Purified water; USP Gluten-free, non-GMO, organic cane alcohol 20%.

QUESTIONS SECTION

newtonlabs.net - Questions? 800 448-7256

Newton Laboratories, Inc. FDA Est # 1051203 - Conyers, GA 30013

INDICATIONS & USAGE SECTION

Formulated for associated symptoms such as dizziness, fatigue, weakness, tingling and numb or cold extremities.

OTC - PREGNANCY OR BREAST FEEDING SECTION

If pregnant or breast-feeding, ask a doctor before use.